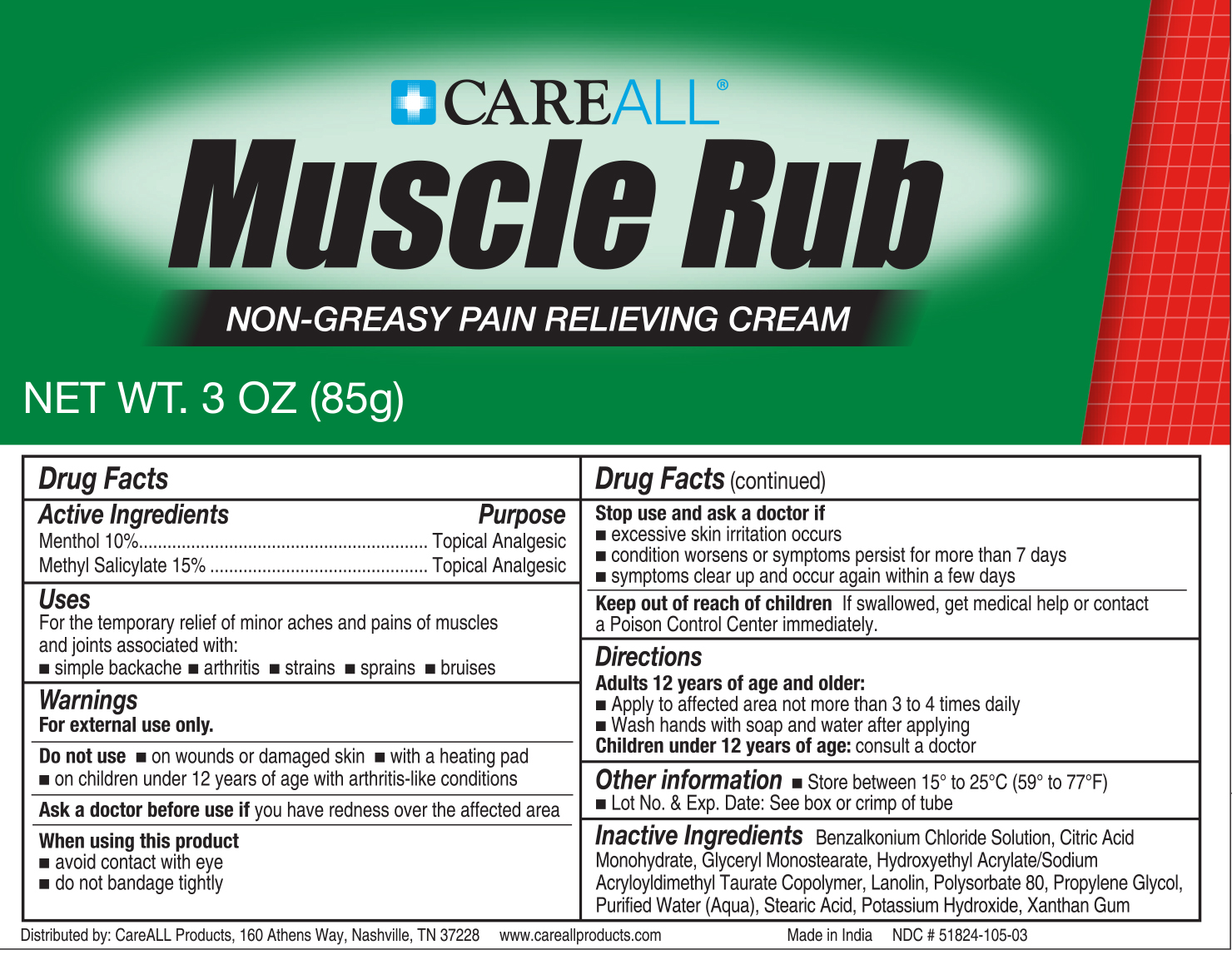 DRUG LABEL: CAREALL Muscle Rub

NDC: 51824-105 | Form: CREAM
Manufacturer: New World Imports, Inc
Category: otc | Type: HUMAN OTC DRUG LABEL
Date: 20251201

ACTIVE INGREDIENTS: LEVOMENTHOL 100 mg/1 g; METHYL SALICYLATE 150 mg/1 g
INACTIVE INGREDIENTS: BENZALKONIUM CHLORIDE; CITRIC ACID MONOHYDRATE; GLYCERYL MONOSTEARATE; HYDROXYETHYL ACRYLATE/SODIUM ACRYLOYLDIMETHYL TAURATE COPOLYMER (100000 MPA.S AT 1.5%); LANOLIN; POLYSORBATE 80; PROPYLENE GLYCOL; WATER; STEARIC ACID; POTASSIUM HYDROXIDE; XANTHAN GUM

Drug Facts

ACTIVE INGREDIENT

Menthol

Methyl Salicylate

PURPOSE

Topical analgesic

Keep out of reach of children.If swallowed, get medical help or contact a Poison Control Center Immediately.

INDICATIONS AND USAGE

For the temporary relief of minor aches and pains of muscles and joints associated with simple backache, arthritis, strains, bruises, and sprains.

WARNINGS

For external use only

Do not use:

On wounds or damaged skin

With a heating pad

On a child under 12 years of age with arthritis-like conditions

Ask a doctor before use if

you have redness over the affected area

When using this product

Avoid contact with eyes

Do not bandage tightly

Stop use and ask a doctor if

Condition worsens or symptoms persist for more than 7 days

Symptoms clear up and occur again within a few days

Excessive skin irritation occurs

DOSAGE AND ADMINISTRATION

Adults 12 years of age and older:

apply to affected area not more than 3 to 4 times daily

wash hands with soap and water after apply

Children under 12 years of age:ask a doctor

INACTIVE INGREDIENT

Benzalkonium Chloride Solution, Citric Acid Monohydrate, Glyceryl Monostearate, Hydroxyethyl Acrylate/Sodium Acryloyldimethyl Taurate Copolymer, Lanolin, Polysorbate 80, Propylene Glycol, Purified Water (Aqua), Stearic Acid, Potassium Hydroxide, Xanthan Gum